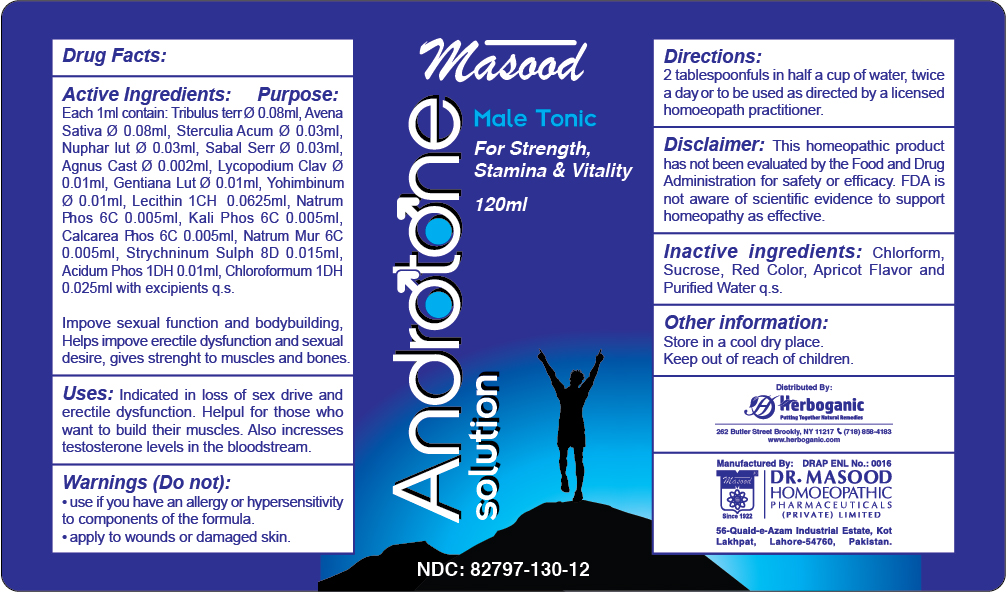 DRUG LABEL: Androtone syrup
NDC: 82797-130 | Form: SYRUP
Manufacturer: Dr. Masood Homeopathic Pharmaceuticals Private Limited
Category: homeopathic | Type: HUMAN OTC DRUG LABEL
Date: 20240708

ACTIVE INGREDIENTS: TRIBULUS TERRESTRIS WHOLE 0.08 mg/120 mL; GENTIANA LUTEA WHOLE 0.01 mg/120 mL; YOHIMBINE 0.01 mg/120 mL; AVENA SATIVA WHOLE 0.08 mg/120 mL; SABAL PALMETTO WHOLE 0.03 mg/120 mL; VITEX AGNUS-CASTUS WHOLE 0.02 mg/120 mL; LYCOPODIUM CLAVATUM WHOLE 0.01 mg/120 mL; CALCIUM PHOSPHATE 0.005 mg/120 mL; COLA ACUMINATA WHOLE 0.03 mg/120 mL; NUPHAR LUTEA WHOLE 0.03 mg/120 mL; SODIUM CHLORIDE 0.005 mg/120 mL; MONOBASIC POTASSIUM PHOSPHATE 0.005 mg/120 mL; PHOSPHORIC ACID 0.01 mg/120 mL; SODIUM PHOSPHATE 0.005 mg/120 mL; STRYCHNINE 0.015 mg/120 mL; LECITHIN, SOYBEAN 0.0625 mg/120 mL
INACTIVE INGREDIENTS: WATER 120 mL/120 mL; SUCROSE 60 mg/120 mL

Dosage and Administration

2 tablespoonful twice daily in half a cup of water or as directed by a licensed homeopathic practitioner

Indications and Usage

Indicated in loss of sex drive and erectile dysfunction.

Helpful for those who want to build their muscles.

Also increases testosterone levels in the bloodstream

Inactive Ingredients

Chlorform

Sucrose

Water

Active Ingredients

TRIBULUS TERRESTRIS

AVENA SATIVA

STERCULIA ACUMINATA (COLA ACCUMINATA)

NUPHAR LUT

SABAL SERRULATE (SABAL PALMETTO)

VITEX AGNUS CASTUS

LYCOPODIUM CLAVATUM

GENTIANA LUT

YOHIMBIN

LECITHIN

SODIUM PHOSPHATE

POTASSIUM PHOSPHATE

CALCIUM PHOSPHATE

STRYCHNIN

SODIUM CHLORIDE

PHOSPHORIC ACID

Keep out of the reach of children

Keep this and all other medicines out of the reach of children

Purpose

Ingredient Purpose

TRIBULUS TERRESTRIS Improves sexual function and for body building

AVENA SATIVA Convalescence, sexual debility and impotency

STERCULIA ACUMINATA Improves circulation to the specific organ and helps improve erectile dysfunction

NUPHAR LUT Causes erection and an increase in sexual desire in those suffering from impotency

SABAL SERRULATE Helps improve loss of sexual power and sexual debility due to prostate problems

AGNUS CASTUS Helps improve erectile dysfunction and sexual desire

LYCOPODIUM CLAVATUM Indicated in impotence and premature ejaculation

GENTIANA LUT Acts as a tonic, causing an increase in appetite

YOHIMBIN Indicated in Neurasthenia and impotence, as an aphrodisiac

LECITHIN helpful in mental exhaustion and impotency

SODIUM PHOSPHATE Indicated in weakness and increased desire without erection

POTASSIUM PHOSPHATE indicated in people suffering from mental & physical depression resulting in diminished sexual power.

CALCIUM PHOSPHATE gives strength to the skeleton (bones) and cures anemia due to acute and chronic wasting diseases.

STRYCHNIN Used to reduce the inflammation of testicles

Warnings

Do not:

use if you have an allergy or hypersensitivity to components of the formula

Stop use and ask a doctor if:

condition worsens
If symptoms persists for more than 7 days